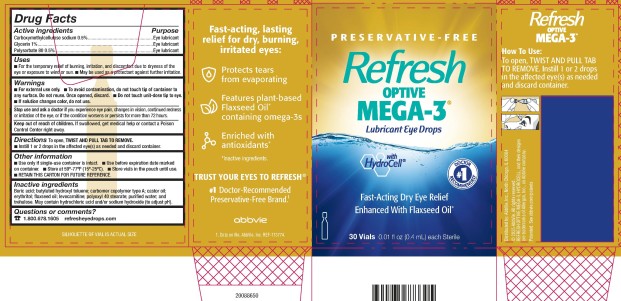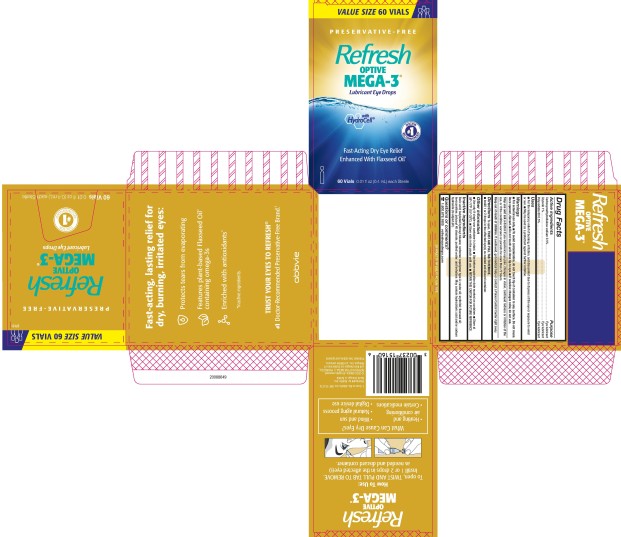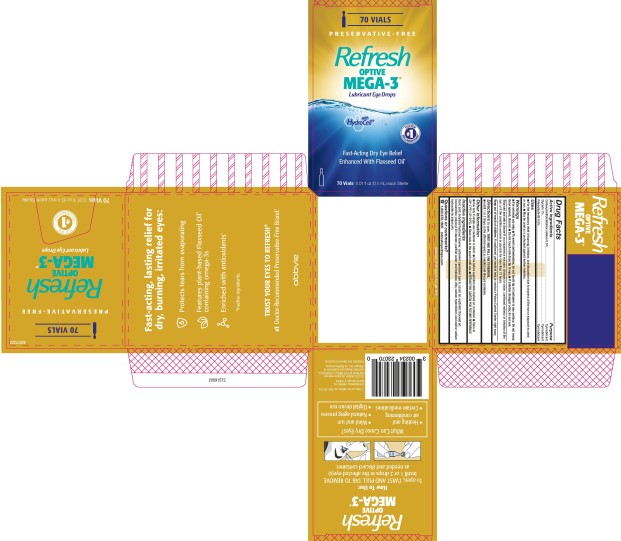 DRUG LABEL: REFRESH Optive Mega-3
NDC: 0023-7151 | Form: SOLUTION/ DROPS
Manufacturer: Allergan, Inc.
Category: otc | Type: HUMAN OTC DRUG LABEL
Date: 20220630

ACTIVE INGREDIENTS: CARBOXYMETHYLCELLULOSE SODIUM 5 mg/1 mL; GLYCERIN 10 mg/1 mL; POLYSORBATE 80 5 mg/1 mL
INACTIVE INGREDIENTS: BORIC ACID; BUTYLATED HYDROXYTOLUENE; CARBOMER COPOLYMER TYPE A (ALLYL PENTAERYTHRITOL CROSSLINKED); CASTOR OIL; ERYTHRITOL; LINSEED OIL; LEVOCARNITINE; POLYOXYL STEARATE 40; WATER; TREHALOSE

REFRESH OPTIVE MEGA-3® (Preservative-free)
Drug Facts

Active ingredients

Carboxymethylcellulose sodium 0.5%
Glycerin 1%
Polysorbate 80 0.5%

Purpose

Eye lubricant
Eye lubricant
Eye lubricant

Uses

- For the temporary relief of burning, irritation, and discomfort due to dryness of the eye or exposure to wind or sun.
- May be used as a protectant against further irritation.

Warnings

- For external use only.
- To avoid contamination, do not touch tip of container to any surface. Do not reuse. Once opened, discard.
- Do not touch unit-dose tip to eye.
- If solution changes color, do not use.

Stop use and ask a doctor if

you experience eye pain, changes in vision, continued redness or irritation of the eye, or if the condition worsens or persists for more than 72 hours.

Keep out of reach of children.

If swallowed, get medical help or contact a Poison Control Center right away.

Directions

To open, TWIST AND PULL TAB TO REMOVE.

- Instill 1 or 2 drops in the affected eye(s) as needed and discard container.

Other information

- Use only if single-use container is intact.
- Use before expiration date marked on container.
- Store at 59°-77°F (15°-25°C).
- Store vials in the pouch until use.
- RETAIN THIS CARTON FOR FUTURE REFERENCE.

Inactive ingredients

Boric acid; butylated hydroxyl toluene; carbomer copolymer type A; castor oil; erythritol; flaxseed oil; levocarnitine; polyoxyl 40 stearate; purified water; and trehalose. May contain hydrochloric acid and/or sodium hydroxide (to adjust pH).

Questions or comments?

1.800.678.1605

refresheyedrops.com

v2.0DFL5773

PRINCIPAL DISPLAY PANEL

NDC 0023-5773-30
PRESERVATIVE - FREE
Refresh
OPTIVE
MEGA-3®
Lubricant Eye Drops
with

HydroCell®

Fast-Acting Dry Eye Relief
Enhanced With Flaxseed Oil*

30 Vials 0.01 fl oz (0.4 mL) each Sterile

PRINCIPAL DISPLAY PANEL

NDC 0023-7151-60
VALUE SIZE 60 VIALS
PRESERVATIVE - FREE
Refresh
OPTIVE
MEGA-3®
Lubricant Eye Drops

With
HydroCell®

Fast-Acting Dry Eye Relief
Enhanced With Flaxseed Oil*

60 Vials 0.01 fl oz (0.4 mL) each Sterile

PRINCIPAL DISPLAY PANEL

NDC 0023-4230-70
70 VIALS
PRESERVATIVE – FREE
Refresh
OPTIVE
MEGA-3®
Lubricant Eye Drops

with
HydroCell®

Fast-Acting Dry Eye Relief
Enhanced with Flaxseed Oil*

70 Vials 0.01 fl oz (0.4 mL) each Sterile